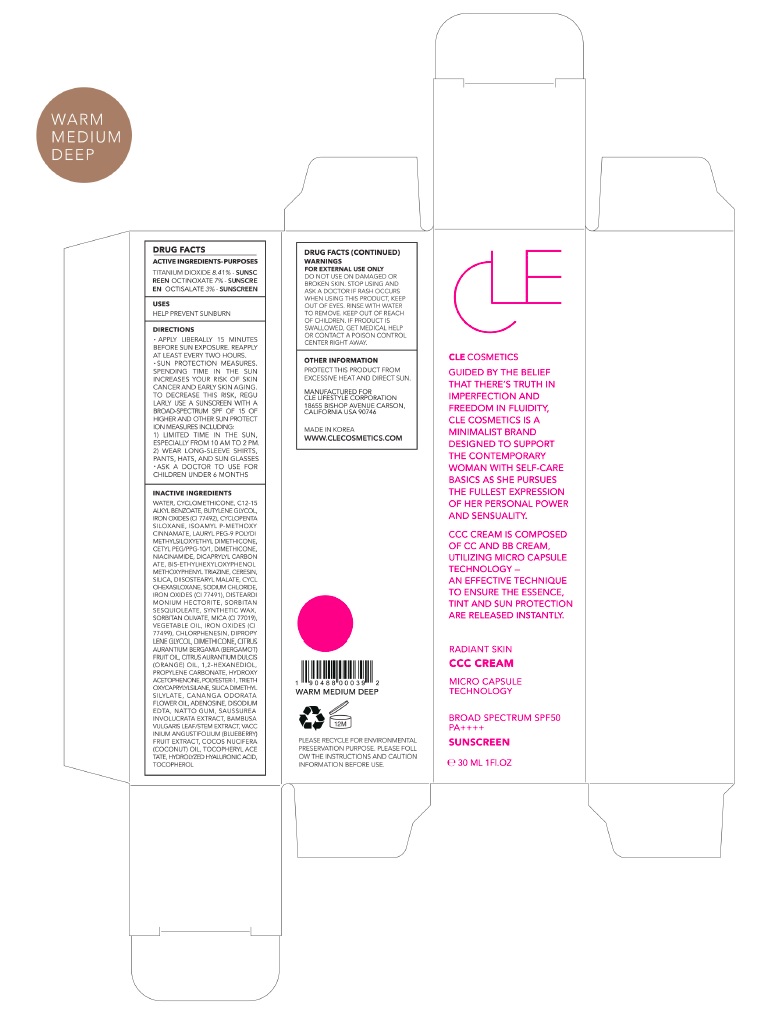 DRUG LABEL: CLE CCC Warm Medium Deep
NDC: 69231-026 | Form: CREAM
Manufacturer: KW ABSC, INC.
Category: otc | Type: HUMAN OTC DRUG LABEL
Date: 20181129

ACTIVE INGREDIENTS: OCTINOXATE 2.1 mg/30 mL; OCTISALATE 0.9 mg/30 mL; TITANIUM DIOXIDE 2.5215 mg/30 mL
INACTIVE INGREDIENTS: WATER; CYCLOMETHICONE; ALKYL (C12-15) BENZOATE; FERRIC OXIDE YELLOW; BUTYLENE GLYCOL; CYCLOMETHICONE 5; AMILOXATE; LAURYL PEG-9 POLYDIMETHYLSILOXYETHYL DIMETHICONE; CETYL PEG/PPG-10/1 DIMETHICONE (HLB 2); NIACINAMIDE; DICAPRYLYL CARBONATE; BEMOTRIZINOL; CERESIN; DIISOSTEARYL MALATE; CYCLOMETHICONE 6; SODIUM CHLORIDE; FERRIC OXIDE RED; DISTEARDIMONIUM HECTORITE; SORBITAN SESQUIOLEATE; SYNTHETIC WAX (1200 MW); SORBITAN OLIVATE; MICA; CORN OIL; FERROSOFERRIC OXIDE; CHLORPHENESIN; DIPROPYLENE GLYCOL; DIMETHICONE; BERGAMOT OIL; ORANGE OIL; 1,2-HEXANEDIOL; PROPYLENE CARBONATE; HYDROXYACETOPHENONE; TRIETHOXYCAPRYLYLSILANE; SILICA DIMETHYL SILYLATE; CANANGA OIL; ADENOSINE; EDETATE DISODIUM ANHYDROUS

69231-026_CCC Warm Medium Deep

ACTIVE INGREDIENT

Titanium Dioxide 8.41%

Ethylhexyl Methoxycinnamate 7.00%

Ethylhexyl Salicylate 3.00%

PURPOSE

Sunscreen

INDICATIONS AND USAGE

Helps prevent sunburn

DOSAGE AND ADMINISTRATION

Apply liberally 15 minutes before sun exposure. Reapply at least every two hours

Sun protection measures. Spending time in the sun increases your risk of skin cancer and early skin aging. To decrease this risk, regularly use a sunscreen with a broad spectrum SPF of 15 of higher and other sun protection measures including: 1) Limited time in the sun, especially from 10 am to 2 pm. 2) Wear long-sleeve shirts, pants, hats, and sunglasses
Ask a doctor to use for children under 6 months

WARNINGS

For external use only.
Do not use on damaged or broken skin.
When using this product, keep out of eyes. Rinse with water to remove.
Stop using and ask a doctor if rash occurs.

KEEP OUT OF REACH OF CHILDREN

Keep out of reach of the children. If product is swallowed, get medical help or contact a poison control center right away.

INACTIVE INGREDIENT

Water, Cyclomethicone, C12-15 Alkyl Benzoate, Butylene Glycol, Iron Oxides (CI 77492), Cyclopentasiloxane, Isoamyl p-Methoxycinnamate, Lauryl PEG-9 Polydimethylsiloxyethyl Dimethicone, Cetyl PEG/PPG-10/1, Dimethicone, Niacinamide, Dicaprylyl Carbonate, Bis-Ethylhexyloxyphenol Methoxyphenyl Triazine, Ceresin, Silica, Diisostearyl Malate, Cyclohexasiloxane, Sodium Chloride, Iron Oxides (CI 77491), Disteardimonium Hectorite, Sorbitan Sesquioleate, Synthetic Wax, Sorbitan Olivate, Mica (CI 77019), Vegetable Oil, Iron Oxides (CI 77499), Chlorphenesin, Dipropylene Glycol, Dimethicone, Citrus Aurantium Bergamia (Bergamot) Fruit Oil, Citrus Aurantium Dulcis (Orange) Oil, 1,2-Hexanediol, Propylene Carbonate, Hydroxyacetophenone, Polyester-1, Triethoxycaprylylsilane, Silica Dimethyl Silylate, Cananga Odorata Flower Oil, Adenosine, Disodium EDTA, Natto Gum, Saussurea Involucrata Extract, Bambusa Vulgaris Leaf/Stem Extract, Vaccinium Angustifolium (Blueberry) Fruit Extract, Cocos Nucifera (Coconut) Oil, Tocopheryl Acetate, Hydrolyzed Hyaluronic Acid, Tocopherol